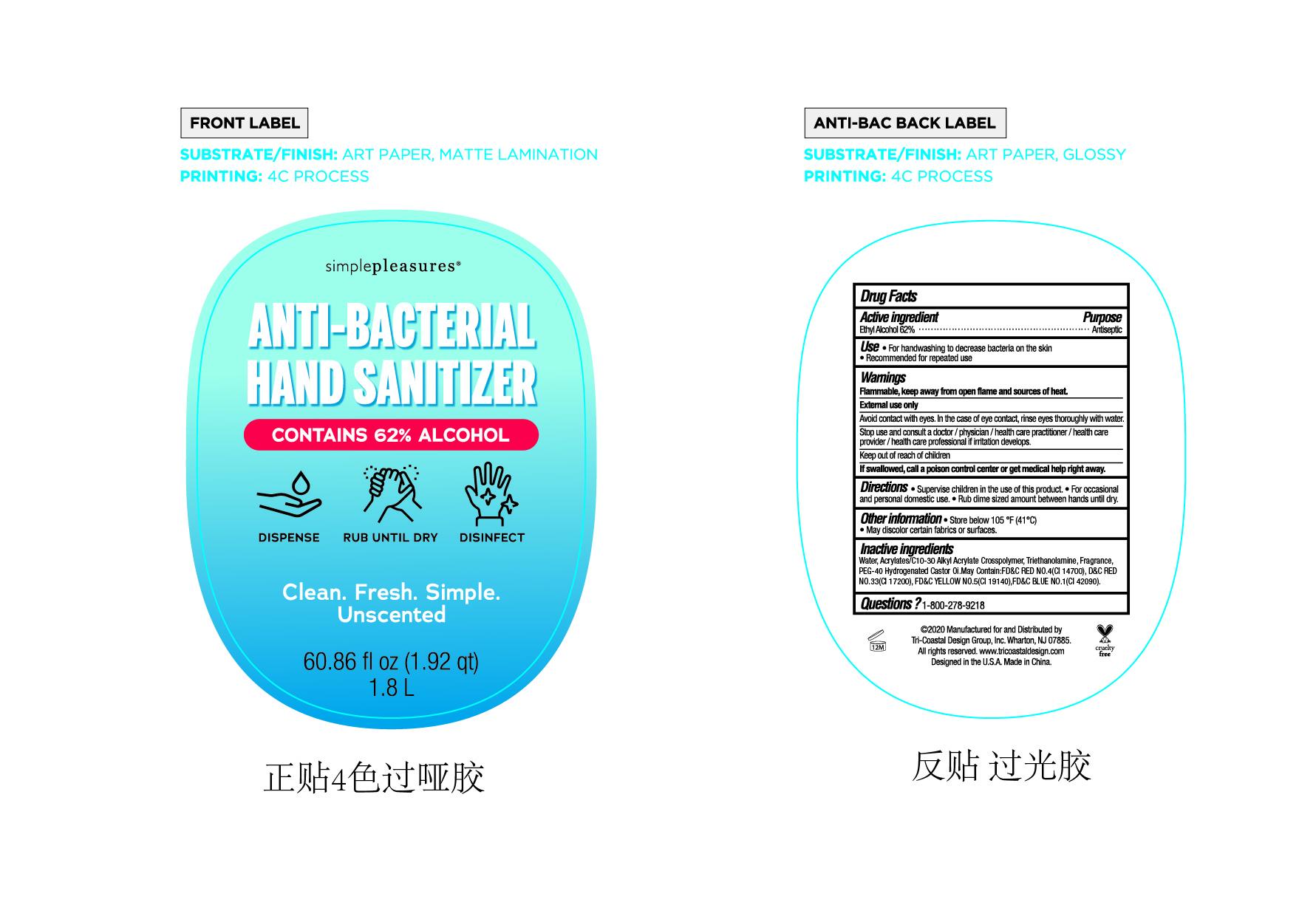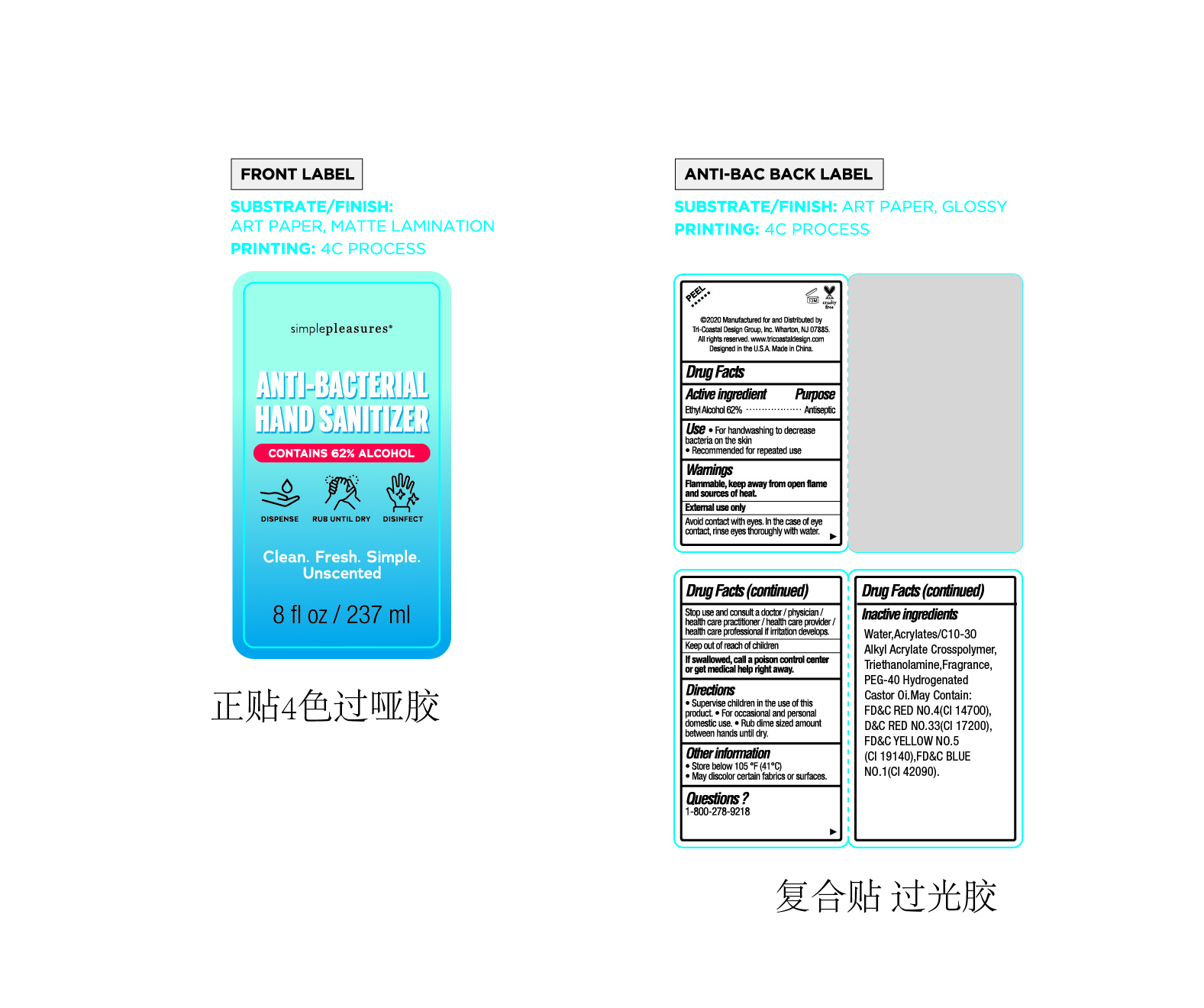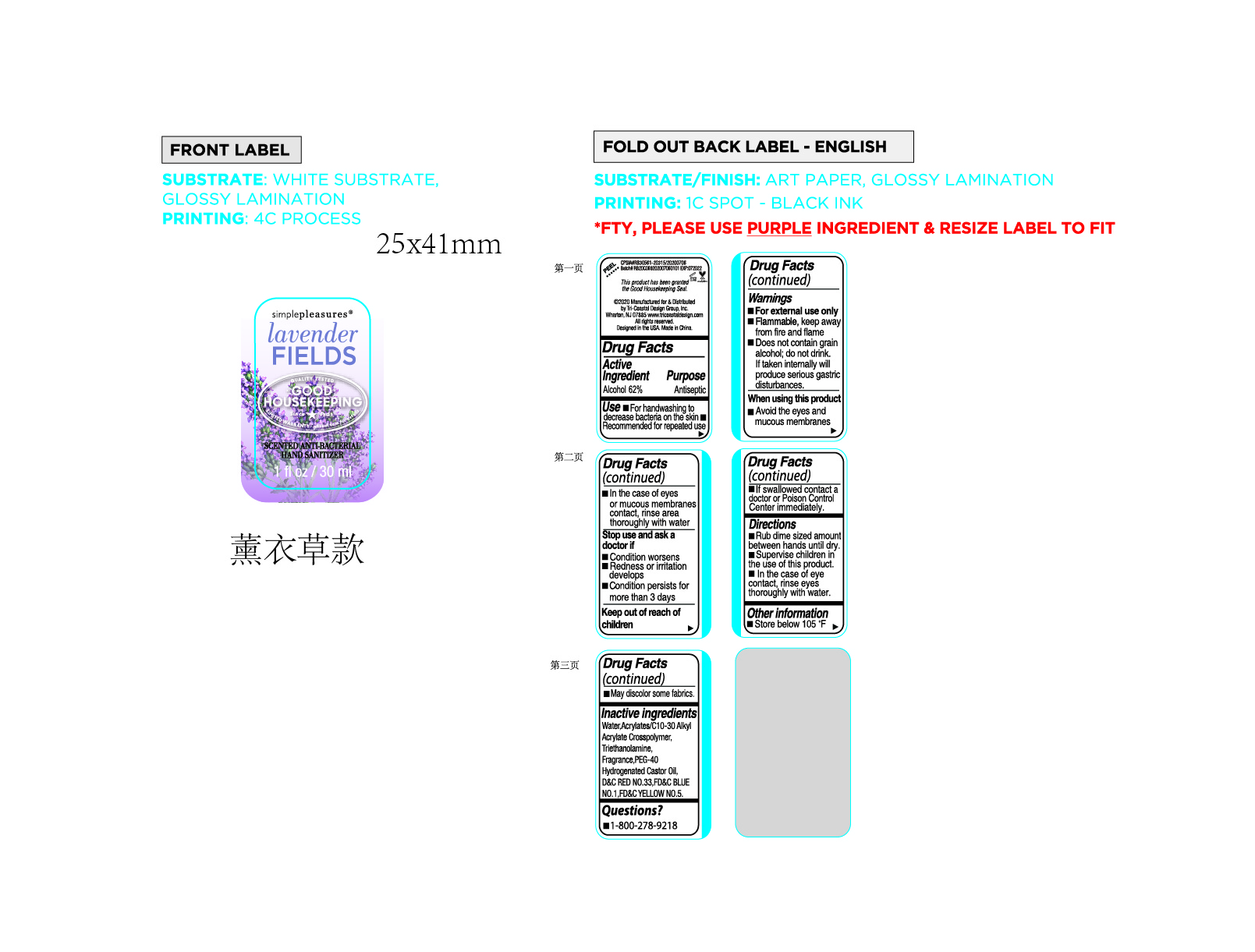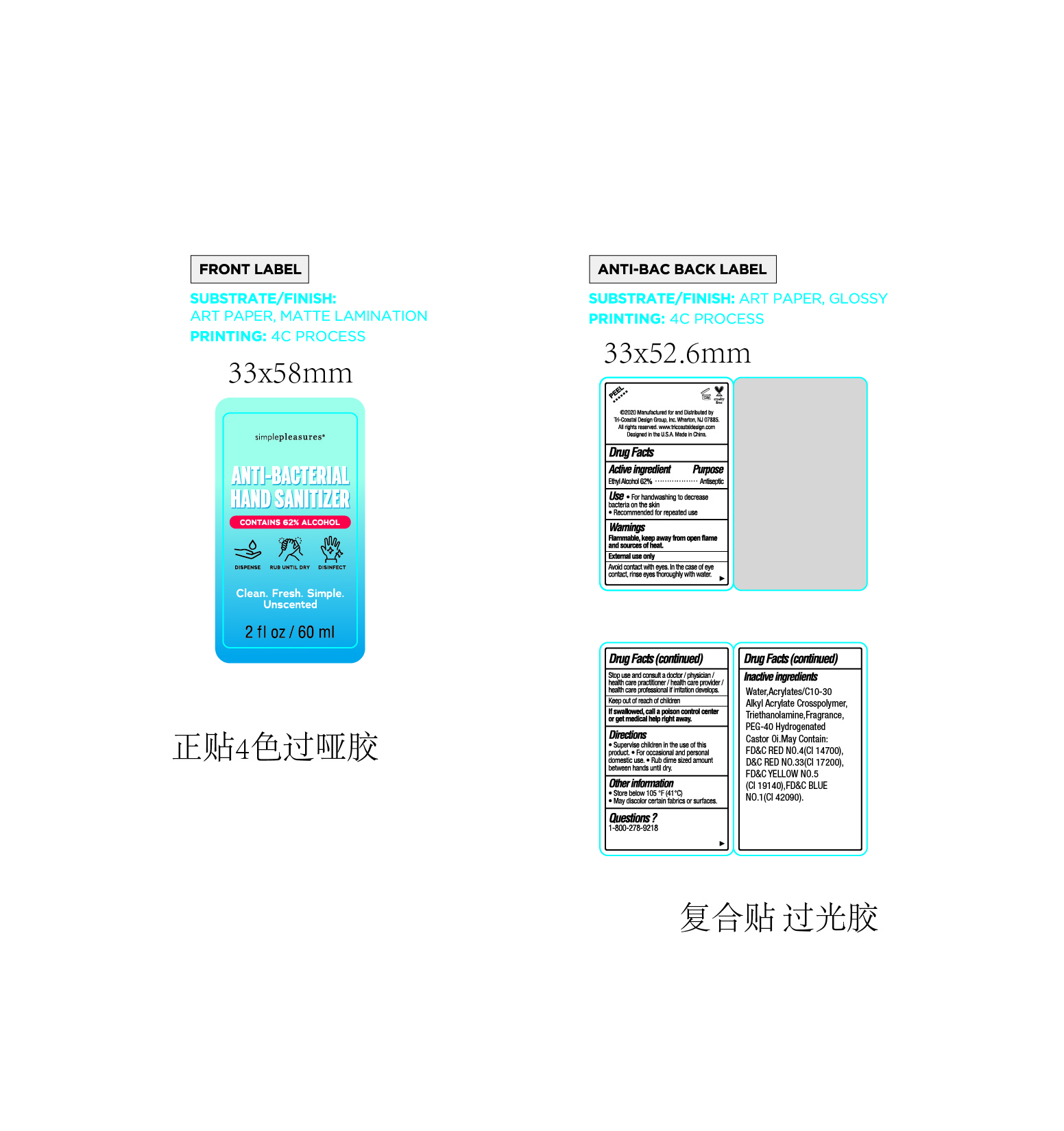 DRUG LABEL: HAND SANITIZER
NDC: 73549-008 | Form: GEL
Manufacturer: Fortress Expert Co., Ltd
Category: otc | Type: HUMAN OTC DRUG LABEL
Date: 20200723

ACTIVE INGREDIENTS: ALCOHOL 62 mL/100 mL
INACTIVE INGREDIENTS: D&C RED NO. 33; FD&C BLUE NO. 1; FD&C RED NO. 4; POLYOXYL 40 HYDROGENATED CASTOR OIL; WATER; TROLAMINE; CARBOMER INTERPOLYMER TYPE A (ALLYL SUCROSE CROSSLINKED); FD&C YELLOW NO. 5

008 HAND SANITIZER

Active ingredient

Ethyl alcohol 62%

Purpose

Antiseptic

Uses

Helps reduce bacteria that potentially can cause disease

Helps prevent cross contamination on contact

Recommended for repeated use

Warnings

Flammable, keep away from open flame and sources of heat

External use only

Avoid contact with eyes , in the case of eyes contact, rinse eyes thoroughly with water.

Stop use and consult a doctor/ physician/ health care practitioner/ health care provider/ health care professional if irritation develops

Keep out of reach of children

DO NOT USE

Avoid contact with eyes , in the case of eyes contact, rinse eyes thoroughly with water.

Stop use and consult a doctor/ physician/ health care practitioner/ health care provider/ health care professional if irritation develops

Keep out of reach of children

If swallowed, call a poison control center or get medical help right away .

Directions

Wet hands thoroughly with product and rub completely covering hands

·Allow to dry without wiping

·Children under the age of 6 should use with adult supervision

Not recommended for infants

Other information

Store below 105F(41C)

May discolor certain fabrics or surfaces.

Inactive ingredients

Water, Acrylates/C10- Alkyl Acrylate Crosspolymer, Triethanolamine, Fragrance

PEG-40 Hydrogenated Castor Oil. May man FD&C RED NO 4(14700), D& REN0.33(C 17200), FD&C YELLOW NO 5(C 19140), FD&C BLUE NO. 1(CI 42090)